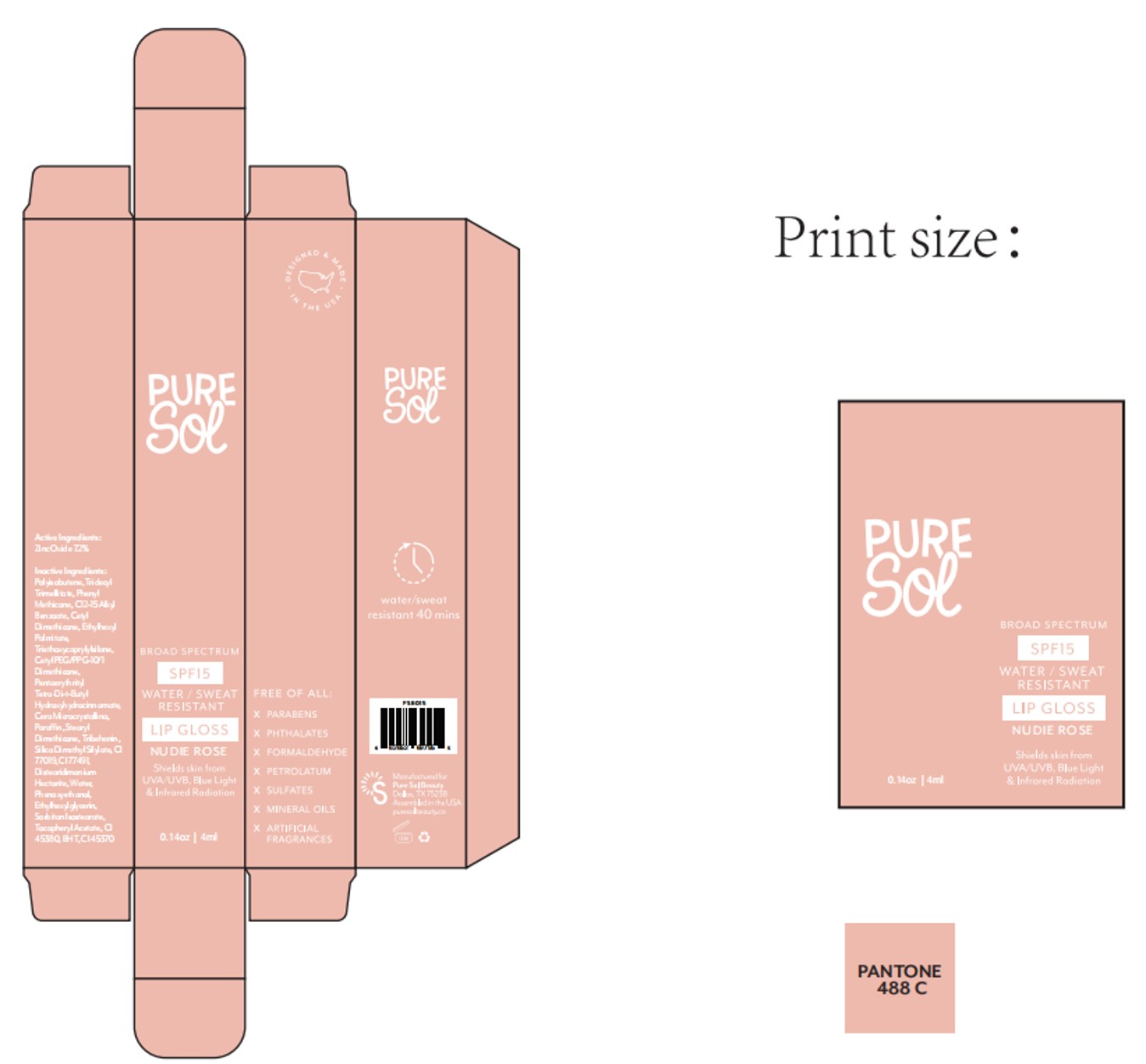 DRUG LABEL: PURE SOL  SPF15  Lip Gloss Nudie rose
NDC: 84090-007 | Form: LIQUID
Manufacturer: Brand 2022b LLC
Category: otc | Type: HUMAN OTC DRUG LABEL
Date: 20251004

ACTIVE INGREDIENTS: ZINC OXIDE 7.2 g/100 mL
INACTIVE INGREDIENTS: CETYL PEG/PPG-10/1 DIMETHICONE (HLB 2); CI 45370; STEARYL TRISILOXANE; BHT; ALPHA-TOCOPHEROL ACETATE; PARAFFIN; HYDROGENATED POLYISOBUTENE 8; MICA; CI 45380; C12-15 ALKYL BENZOATE; TRIDECYL TRIMELLITATE; TRIBEHENIN; PENTAERYTHRITYL TETRA-DI-T-BUTYL HYDROXYHYDROCINNAMATE; MICROCRYSTALLINE WAX; PHENYL METHICONE (500 CST); WATER; PHENOXYETHANOL; TRIETHOXYCAPRYLYLSILANE; CETYL DIMETHICONE/BIS-VINYLDIMETHICONE CROSSPOLYMER; SILICA DIMETHYL SILYLATE; DISTEARDIMONIUM HECTORITE; ETHYLHEXYLGLYCERIN; ETHYLHEXYL PALMITATE; SILICA; CI 77491; SORBITAN ISOSTEARATE; FLAVOR SPICE MINT N&A110589

ACTIVE INGREDIENT

Zinc Oxide 7.2%

PURPOSE

Helps prevent sunburn.

Keep out of reach of children.

If swallowed, get medical help or contact a Poison Control Center right away.

INDICATIONS AND USAGE

■Apply liberally and evenly 15 minutes before sun exposure.

■Reapply at least every two hours.

■Sun Protection Measures: Spending time in the sun increases

your risk of skin cancer and early skin aging. To decrease this risk,

regularly use a sunscreen with a Broad Spectrum SPF value of 15

or higher and other sun protection measures including:

• limit time in the sun, especially from 10 AM – 2 PM

• wear long sleeve shirts, pants, hats, and sunglasses

DOSAGE AND ADMINISTRATION

■Apply liberally and evenly 15 minutes before sun exposure.

■Reapply at least every two hours.

■Sun Protection Measures: Spending time in the sun increases

INACTIVE INGREDIENT

POLYISOBUTENE
TRIDECYL TRIMELLITATE
PHENYL METHICONE
C12-15 ALKYL BENZOATE
CETYL DIMETHICONE
ETHYLHEXYL PALMITATE
SILICA
TRIETHOXYCAPRYLYLSILANE
CETYL PEG/PPG-10/1 DIMETHICONE
PENTAERYTHRITYL TETRA-DI-t-BUTYL HYDROXYHYDROCINNAMATE
CERA MICROCRISTALLINA
PARAFFIN
STEARYL DIMETHICONE
TRIBEHENIN
CERA MICROCRISTALLINA
FLAVOR
SILICA DIMETHYL SILYLATE
CI 77019
CI 77491
DISTEARDIMONIUM HECTORITE
WATER
PHENOXYETHANOL
ETHYLHEXYLGLYCERIN
SORBITAN ISOSTEARATE
TOCOPHERYL ACETATE
CI 45370
BHT
CI 45380

WARNINGS

For external use only

When using this product keep out of eyes.

Rinse with water to remove - do not use on broken skin.